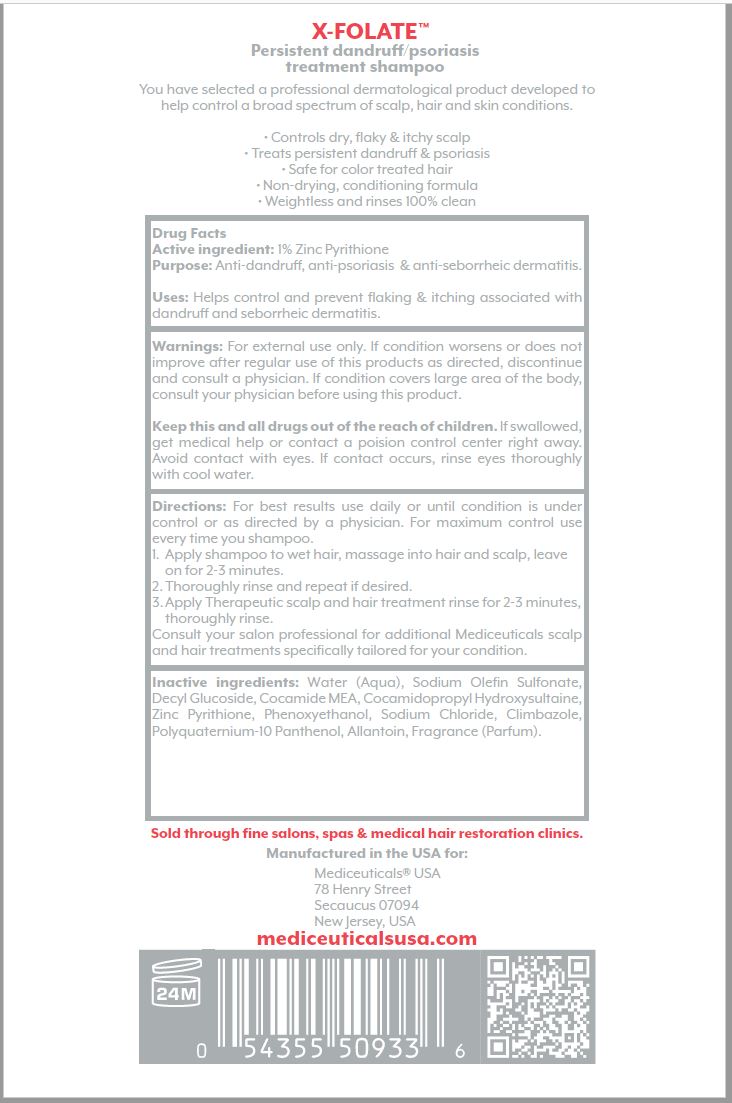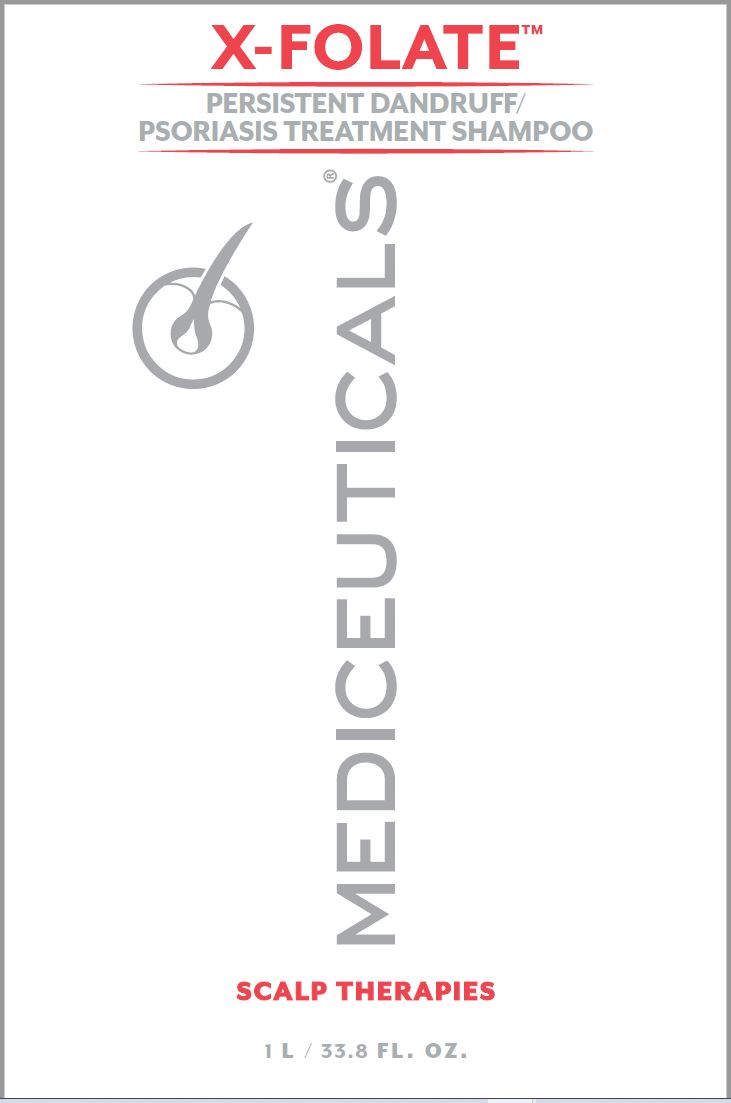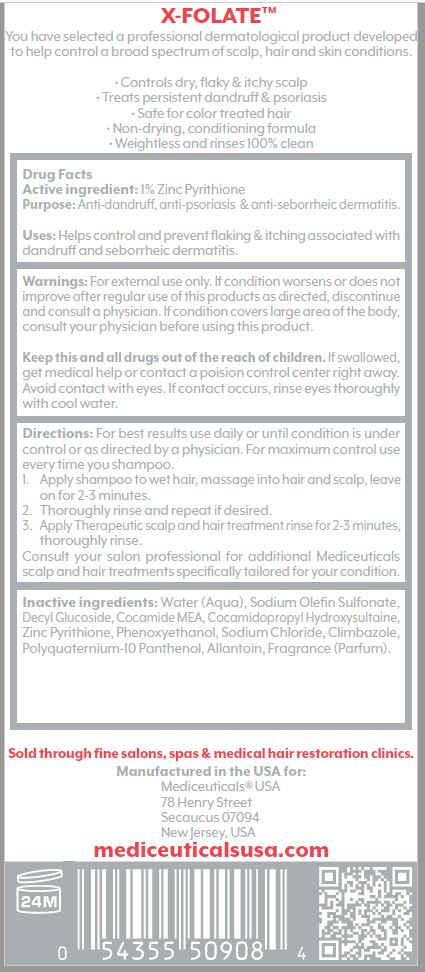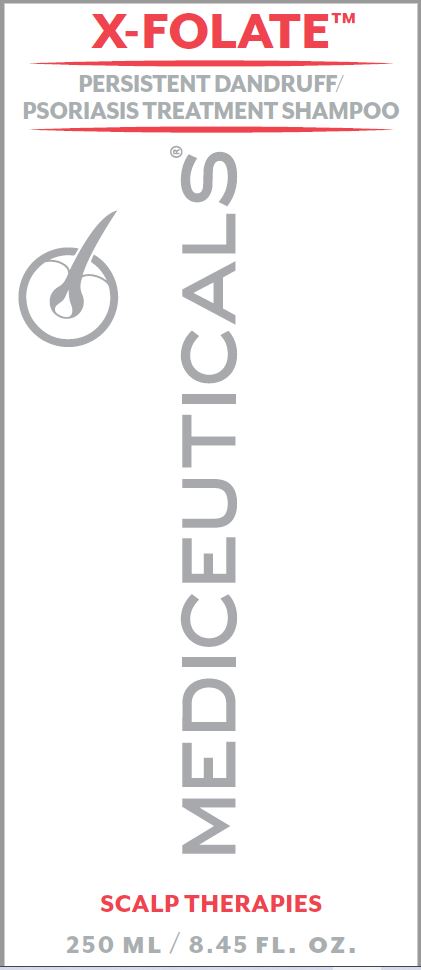 DRUG LABEL: X FOLATE
NDC: 59279-506 | Form: SHAMPOO
Manufacturer: Mediceutical Laboratories, LTD
Category: otc | Type: HUMAN OTC DRUG LABEL
Date: 20220113

ACTIVE INGREDIENTS: PYRITHIONE ZINC 1 g/100 mL
INACTIVE INGREDIENTS: WATER; SODIUM C14-16 OLEFIN SULFONATE; DECYL GLUCOSIDE; COCO MONOETHANOLAMIDE; COCAMIDOPROPYL HYDROXYSULTAINE; PHENOXYETHANOL; SODIUM CHLORIDE; CLIMBAZOLE; POLYQUATERNIUM-10 (1000 MPA.S AT 2%); PANTHENOL; ALLANTOIN

Mediceutical Laboratories - MEDICEUTICALS X-FOLATE (59279-506)

ACTIVE INGREDIENT

1% ZINC PYRITHIONE

PURPOSE

Anti-dandruff, anti-psoriasis & anti-seborrheic dermatitis.

USES

Helps control and prevent flaking & itching associated with dandruff and seborrheic dermatitis.

WARNINGS

For external use only. If condition worsens or does not improve after regular use of this products as directed, discontinue
and consult a physician. If condition covers large area of the body, consult your physician before using this product.

KEEP OUT OF REACH OF CHILDREN

Keep this and all drugs out of the reach of children. If swallowed, get medical help or contact a poision control center right away. Avoid contact with eyes. If contact occurs, rinse eyes thoroughly with cool water.

DIRECTIONS

For best results use daily or until condition is under control or as directed by a physician. For maximum control use every time you shampoo.

1. Apply shampoo to wet hair, massage into hair and scalp, leave on for 2-3 minutes.
2. Thoroughly rinse and repeat if desired.
3. Apply Therapeutic scalp and hair treatment rinse for 2-3 minutes, thoroughly rinse.

Consult your salon professional for additional Mediceuticals scalp and hair treatments specifically tailored for your condition.

INACTIVE INGREDIENTS

Water (Aqua), Sodium Olefin Sulfonate, Decyl Glucoside, Cocamide MEA, Cocamidopropyl Hydroxysultaine, Zinc Pyrithione, Phenoxyethanol, Sodium Chloride, Climbazole, Polyquaternium-10 Panthenol, Allantoin, Fragrance (Parfum).